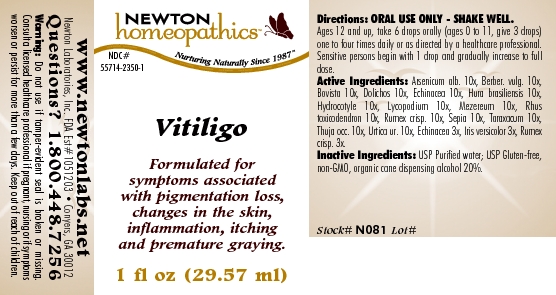 DRUG LABEL: Vitiligo 
NDC: 55714-2350 | Form: LIQUID
Manufacturer: Newton Laboratories, Inc.
Category: homeopathic | Type: HUMAN OTC DRUG LABEL
Date: 20110301

ACTIVE INGREDIENTS: Arsenic Trioxide 10 [hp_X]/1 mL; Berberis Vulgaris Root Bark 10 [hp_X]/1 mL; Giant Puffball 10 [hp_X]/1 mL; Mucuna Pruriens Fruit Trichome 10 [hp_X]/1 mL; Echinacea, Unspecified 10 [hp_X]/1 mL; Hura Crepitans Sap 10 [hp_X]/1 mL; Centella Asiatica 10 [hp_X]/1 mL; Lycopodium Clavatum Spore 10 [hp_X]/1 mL; Daphne Mezereum Bark 10 [hp_X]/1 mL; Toxicodendron Pubescens Leaf 10 [hp_X]/1 mL; Rumex Crispus Root 10 [hp_X]/1 mL; Sepia Officinalis Juice 10 [hp_X]/1 mL; Taraxacum Officinale 10 [hp_X]/1 mL; Thuja Occidentalis Leafy Twig 10 [hp_X]/1 mL; Urtica Urens 10 [hp_X]/1 mL; Iris Versicolor Root 3 [hp_X]/1 mL
INACTIVE INGREDIENTS: Alcohol

Vitiligo

INDICATIONS & USAGE SECTION

Vitiligo Formulated for symptoms associated with pigmentation loss, changes in the skin, inflammation, itching and premature graying.

DOSAGE & ADMINISTRATION SECTION

Directions: ORAL USE ONLY - SHAKE WELL. Ages 12 and up, take 6 drops orally (ages 0 to 11, give 3 drops) one to four times daily or as directed by a healthcare professional. Sensitive persons begin with 1 drop and gradually increase to full dose.

OTC - ACTIVE INGREDIENT SECTION

Arsenicum alb. 10x, Berber. vulg. 10x, Bovista 10x, Dolichos 10x, Echinacea 10x, Hura brasiliensis 10x, Hydrocotyle 10x, Lycopodium 10x, Mezereum 10x, Rhus toxicodendron 10x, Rumex crisp. 10x, Sepia 10x, Taraxacum 10x, Thuja occ. 10x, Urtica ur. 10x, Echinacea 3x, Iris versicolor 3x, Rumex crisp. 3x.

OTC - PURPOSE SECTION

Formulated for symptoms associated with pigmentation loss, changes in the skin, inflammation, itching and premature graying.

INACTIVE INGREDIENT SECTION

Inactive Ingredients: USP Purified Water; USP Gluten-free, non-GMO, organic cane dispensing alcohol 20%.

QUESTIONS SECTION

www.newtonlabs.net Newton Laboratories, Inc. FDA Est # 1051203 - Conyers, GA 30012
Questions? 1.800.448.7256

WARNINGS SECTION

Warning: Do not use if tamper - evident seal is broken or missing. Consult a licensed healthcare professional if pregnant, nursing or if symptoms worsen or persist for more than a few days. Keep out of reach of children.

OTC - PREGNANCY OR BREAST FEEDING SECTION

Consult a licensed healthcare professional if pregnant, nursing or if symptoms worsen or persist for more than a few days.

OTC - KEEP OUT OF REACH OF CHILDREN SECTION

Keep out of reach of children.